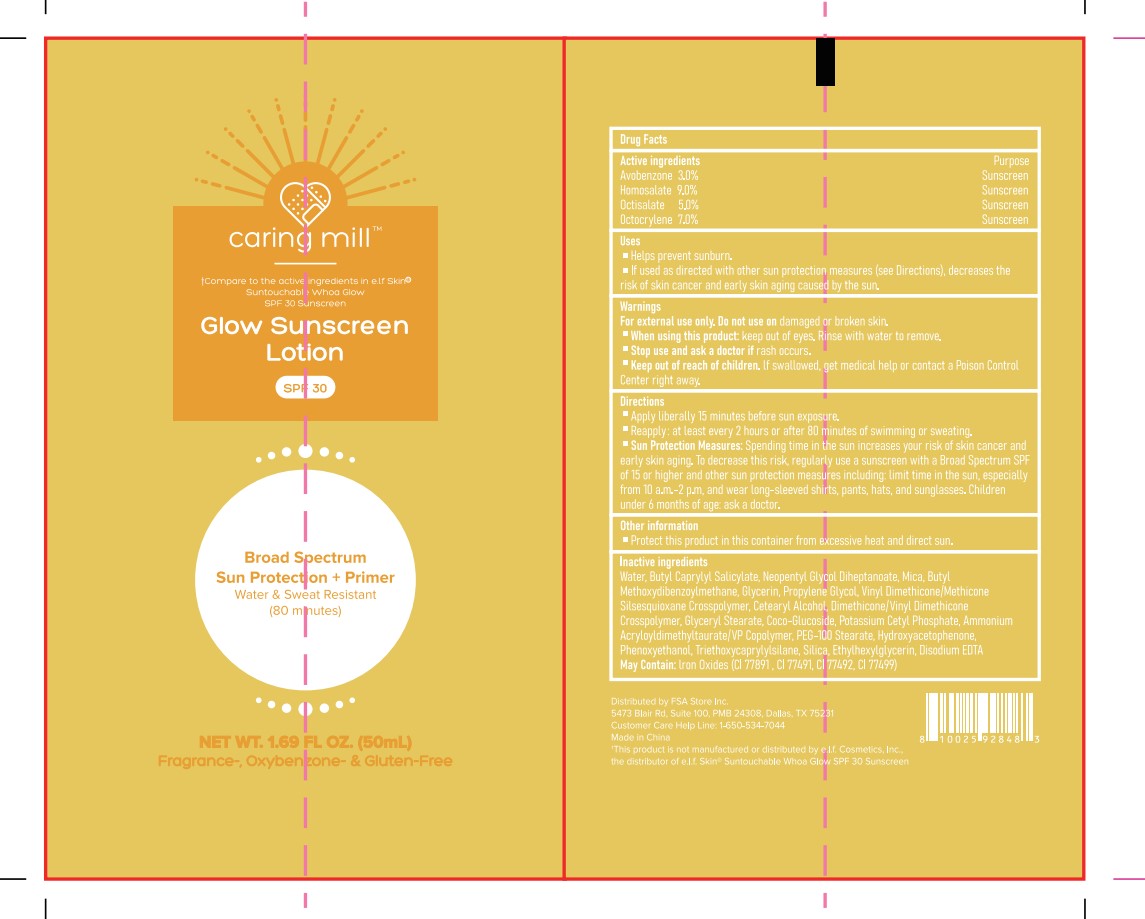 DRUG LABEL: SUNSCREEN GLOWING
NDC: 87283-006 | Form: LOTION
Manufacturer: Aopline Biotechnology (Guangzhou) Co., Ltd.
Category: otc | Type: HUMAN OTC DRUG LABEL
Date: 20260108

ACTIVE INGREDIENTS: OCTOCRYLENE 3.5 g/50 mL; OCTISALATE 2.5 g/50 mL; HOMOSALATE 4.5 g/50 mL; AVOBENZONE 1.5 g/50 mL
INACTIVE INGREDIENTS: POTASSIUM CETYL PHOSPHATE; EDETATE DISODIUM; PROPYLENE GLYCOL; DIMETHICONE/VINYL DIMETHICONE CROSSPOLYMER (HARD PARTICLE); CI 77891; SILICA; MICA; GLYCERIN; COCO GLUCOSIDE; GLYCERYL STEARATE; ETHYLHEXYLGLYCERIN; TRIETHOXYCAPRYLYLSILANE; AMMONIUM ACRYLOYLDIMETHYLTAURATE/VP COPOLYMER; CI 77491; PHENOXYETHANOL; NEOPENTYL GLYCOL DIHEPTANOATE; CI 77492; PEG-100 STEARATE; BUTYLOCTYL SALICYLATE; WATER; FERROSOFERRIC OXIDE; HYDROXYACETOPHENONE; CETOSTEARYL ALCOHOL; VINYL DIMETHICONE/METHICONE SILSESQUIOXANE CROSSPOLYMER

87283-006-01 Sunscreen Glowing

ACTIVE INGREDIENT

AVOBENZONE G63QQF2NOX 3.0%
OCTISALATE 4X49Y0596W 5.0%
OCTOCRYLENE 5A68WGF6WM 7.0%
HOMOSALATE V06SV4M95S 9%

PURPOSE

Sunscreen

Keep out of reach of children. lf swallowed, get medical help or contact a Poison ControlCenter right away

WARNINGS

For external use only. Do not use on damagedor broken skin.
When using this product keep out of eyes.nse with water to remove.
Stop use and ask a doctor if rash occurs.
Keep out of reach of children. lf swallowed, get medical help or contact a Poison ControlCenter right away

DOSAGE AND ADMINISTRATION

Apply liberally 15 minutes before sun exposure.

Reapply: at least every 2 hours or after 80 minutes of swimming or sweating.

Directions
Apply liberally 15 minutes before sun exposure. Reapply: at least every 2 hours or after 80 minutes of swimming or sweating. Sun Protection Measures: $pending time in the sun increases your risk of skin cancer andearly skin aging. To decrease this risk, regularly use a sunscreen with a Broad Spectrum SPfof 15 or higher and other sun protection measures including: limit time in the sun, especiallyfrom 10 a.m.-2 pm, and wear long-sleeved shirts, pants, hats, and sunglasses. Childrenunder 6 months of age ask a doctor.

INACTIVE INGREDIENT

WATER
BUTYLOCTYL SALICYLATE
NEOPENTYL GLYCOL DIHEPTANOATE
MICA
CI 77891
BUTYL METHOXYDIBENZOYLMETHANE
GLYCERIN
PROPYLENE GLYCOL
VINYL DIMETHICONE/METHICONE SILSESQUIOXANE CROSSPOLYMER
CETEARYL ALCOHOL
COCO-GLUCOSIDE
GLYCERYL STEARATE
PEG-100 STEARATE
DIMETHICONE/VINYL DIMETHICONE CROSSPOLYMER
SILICA
POTASSIUM CETYL PHOSPHATE
AMMONIUM ACRYLOYLDIMETHYLTAURATE/VP COPOLYMER
CETEARYL ALCOHOL
HYDROXYACETOPHENONE
PHENOXYETHANOL
ETHYLHEXYLGLYCERIN
CI 77492
TRIETHOXYCAPRYLYLSILANE
DISODIUM EDTA
CI 77491
CI 77499